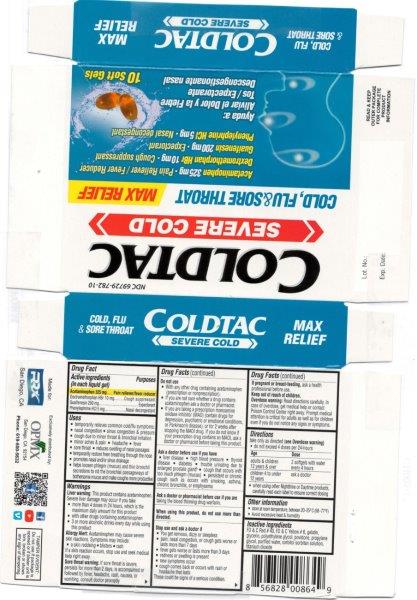 DRUG LABEL: Acetaminophen, Guaifenesin, Dextromethorphan HBr, Phenylephrine HCl
NDC: 69729-782 | Form: CAPSULE, LIQUID FILLED
Manufacturer: OPMX LLC
Category: otc | Type: HUMAN OTC DRUG LABEL
Date: 20240517

ACTIVE INGREDIENTS: ACETAMINOPHEN 325 mg/1 1; GUAIFENESIN 200 mg/1 1; DEXTROMETHORPHAN HYDROBROMIDE 10 mg/1 1; PHENYLEPHRINE HYDROCHLORIDE 5 mg/1 1
INACTIVE INGREDIENTS: POLYETHYLENE GLYCOL 400; GLYCERIN; WATER; FD&C YELLOW NO. 6; PROPYLENE GLYCOL; SORBITOL; POVIDONE K30; GELATIN; SORBITAN

Coldtac Severe
(Acetaminophen 325mg, Dextromethorphan HBr 10mg, Guaifenesin 200mg, Phenylephrine HCl 5mg Softgel)

ACTIVE INGREDIENT

Acetaminophen 325mg

Dextromethorphan HBr 10mg

Guaifenesin 200mg

Phenylephrine HCl 5mg

PURPOSE

Pain reliever/fever reducer

Cough suppressant

Expectorant

Nasal decongestant

INACTIVE INGREDIENT

FD&C red #40, FD&C yellow #6, gelatin, glycerin, polyethylene glycol, povidone, propylene glycol, purified water, sorbitol sorbitan solution, titanium dioxide

DOSAGE AND ADMINISTRATION

- Take only as directed (See overdose warning)
- Do not exceed 4 doses per 24-hours
- Adults and children 12 years and over: take 2 softgels with water every 4 hours
- Children 4 to under 12 years: ask a doctor
- When using other Nighttime or Daytime products, carefully read each label to ensure correct dosing

INDICATIONS AND USAGE

Temporarily relieves common cold/flu symptoms:

- Nasal congestion
- Sinus congestion & pressure
- Cough due to minor throat & bronchial irritation
- Minor aches & pain
- Headache
- Fever
- Sore throat
- Reduces swelling of nasal passages
- Temporarily restore freer breathing through the nose
- Promotes nasal and/or sinus drainage
- Helps loosen phlegm (mucus) and thin bronchial secretions to rid the bronchial passageways of bothersome mucus and make coughs more productive.

WARNINGS

Liver warning: This product contains acetaminophen. Severe liver damage may occur if you take more than 4 doses in 24 hours, which is the maximum daily amount for this product with other drugs contains acetaminophen 3 or more alcoholic drinks every day while using this product.

Allergy alert: Acetaminophen may cause severe skin reactions. Symptoms may include:

skin reddening
blisters
rash

If a skin reaction occurs, stop use and seek medical help right away.

Sore throat warning: if sore throat is severe, persists for more than 2 days, is accompanied or followed by fever, headache, rash, nausea, or vomiting, consult doctor promptly

Do not use:

- with any other drug containing acetaminophen (prescription or nonprescription).
- If you are not sure whether a drug contains acetaminophen, ask a doctor or pharmacist
- If you are now taking a prescription monoamine oxidase inhibitor (MAOI) (certain drugs for depression, psychiatric, or emotional conditions, or Parkinson’s disease), or for 2 weeks after stopping the MAOI drug. If you do not know if your prescription drug contains an MAOI, ask a doctor or pharmacist before taking this product.

Ask a doctor before use if you have:

Liver disease
High blood pressure
Thyroid disease
Diabetes
Trouble urinating due to enlarged prostate gland
Cough that occurs with too much phlegm (mucus)
Persistent or chronic cough such as occurs with smoking, asthma, chronic bronchitis, or emphysema

Ask a doctor or pharmacist before use if you are taking the blood thinning drug warfarin.

When using this product, do not use more than directed.

Stop use and ask a doctor if:

You get nervous, dizzy, or sleepless
Pain, nasal congestion, or cough gets worse or lasts more than 7 days
Fever gets worse or last more than 3 days
Redness or swelling is present
New symptoms occur
Cough comes back or occurs with rash or headache that lasts

These could be signs of a serious condition.

If pregnant or breast-feeding: ask a health professional before use.

Keep out of reach of children.

Keep out of reach of children.

OVERDOSAGE

OVERDOSE WARNING: Read directions carefully. In case of overdose, get medical help or contact a Poison Control Center right away. Prompt medical attention is critical for adults as well as for children even if you do not notice any signs or symptoms.

OTHER SAFETY INFORMATION

store at room temperature between 20-25°C (68-77ºF)

avoid excessive heat and humidity